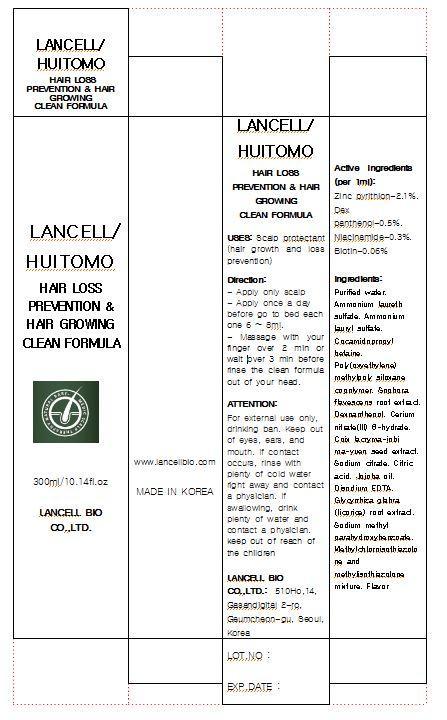 DRUG LABEL: LANCELL HUITOMO HAIR LOSS PREVENTION HAIR GROWER CLEAN FORMULA
NDC: 69388-1001 | Form: LIQUID
Manufacturer: Lancell Bio Co., Ltd.
Category: otc | Type: HUMAN OTC DRUG LABEL
Date: 20141201

ACTIVE INGREDIENTS: PYRITHIONE ZINC 2.1 g/100 mL
INACTIVE INGREDIENTS: WATER; NIACINAMIDE; BIOTIN

Drug Facts

ACTIVE INGREDIENT

zinc pyrithion

INACTIVE INGREDIENT

■ Purified water ■Ammonium laureth sulfate ■Ammonium lauryl sulfate ■Cocamidopropyl betaine ■Poly(oxyethylene) methylpoly siloxane copolymer ■Sophora flavescens root extract ■Dexpanthenol ■Cerium nitrate(III) 6-hydrate ■Coix lacryma-jobi ma-yuen seed extract ■Sodium citrate ■Citric acid ■Jojoba oil ■Disodium EDTA ■Glycyrrhiza glabra (licorice) root extract ■Sodium methyl parahydroxybenzoate ■Methylchloroisothiazolone and methylisothiazolone mixture ■Flavor

PURPOSE

scalp protectant (hair growth and loss prevention)

keep out of reach of the children

INDICATIONS AND USAGE

■ Apply only scalp
■ Apply once a day before go to bed each one 6 ~ 8ml
■ Massage with your finger over 2 min or wait over 3 min before rinse the clean formula out of your head

WARNINGS

For external use only, drinking ban
When using this product
■ keep out of eyes, ears, and mouth. If contact occurs, rinse with plenty of worm or cold water right away and in a serious situation, contact a physician. If swallowing, drink plenty of water and contact a physician
■ Keep out of reach of the children

DOSAGE AND ADMINISTRATION

for external use only